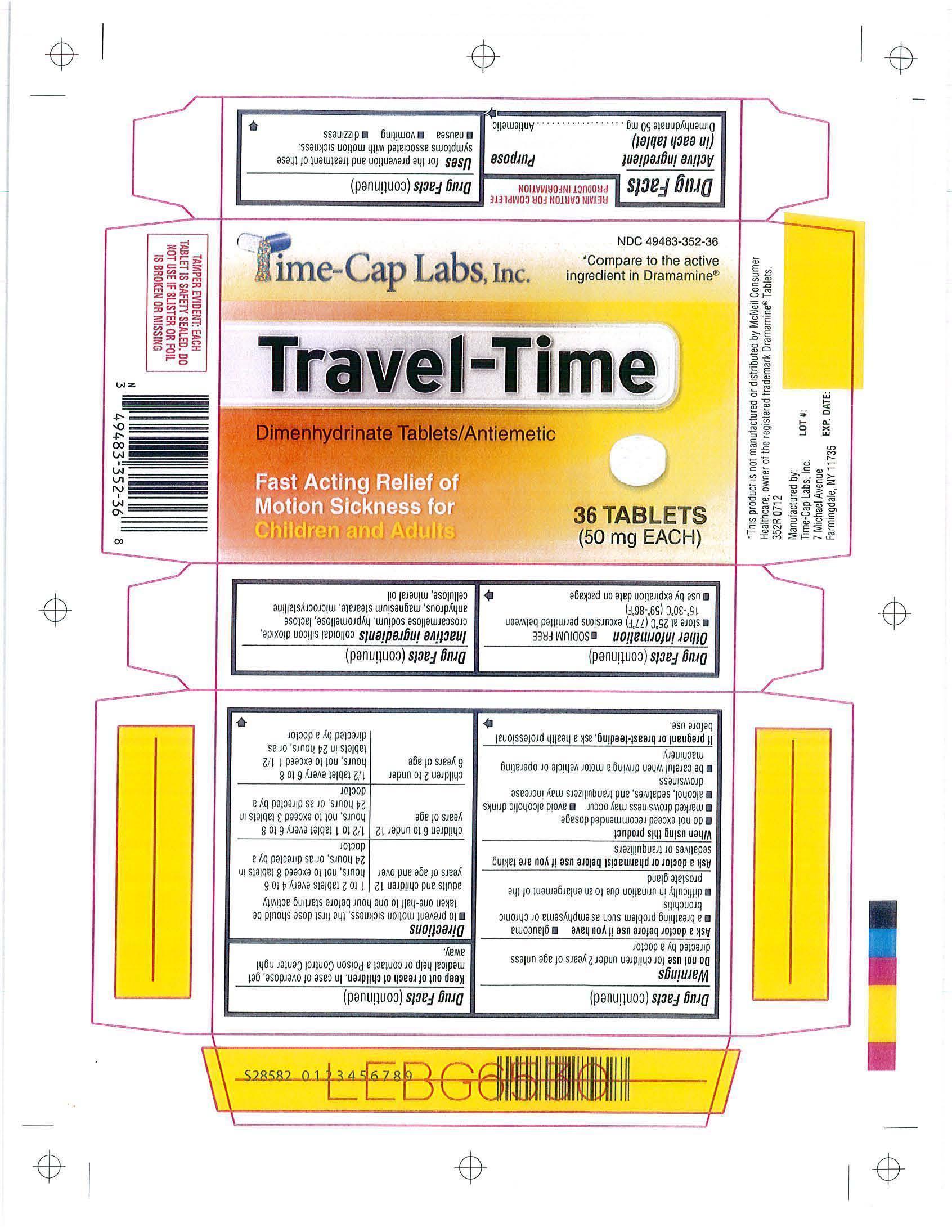 DRUG LABEL: DIMENHYDRINATE 
NDC: 49483-352 | Form: TABLET, FILM COATED
Manufacturer: Time Cap Labs, Inc
Category: otc | Type: HUMAN OTC DRUG LABEL
Date: 20130327

ACTIVE INGREDIENTS: DIMENHYDRINATE 50 mg/1 1
INACTIVE INGREDIENTS: SILICON DIOXIDE; CROSCARMELLOSE SODIUM; HYPROMELLOSES; ANHYDROUS LACTOSE; MAGNESIUM STEARATE; CELLULOSE, MICROCRYSTALLINE; MINERAL OIL

ACTIVE INGREDIENT

EACH TABLET CONTAINS DIMENHYDRINATE 50 MG

INACTIVE INGREDIENT

COLLOIDAL SILICON DIOXIDE, CROSCARMELLOSE SODIUM,HYPROMELLOSE, AHNYDROUS LACTOSE, MAGNESIUM STEARATE, CELLULOSE, MICROCRYSTALLINE, MINEROL

PURPOSE

Antiemetic

Keep out of reach of children. In case of overdose, get medical help or contact a Poison Control Center right away

DOSAGE AND ADMINISTRATION

irections:
To prevent motion sickness, the first dose should be taken one-half to one hour before starting activity.
Adults and children 12 years of age and over - 1 to 2 tablets every 4 to 6 hours, not to exceed 8 tablets in 24 hours, or as directed by a doctor
Children 6 to under 12 years of age 1/2 to 1 tablet every 6 to 8 hours, not to exceed 3 tablets in 24 hours, or as directed by a doctor
Children 2 to under 6 years of age - 1/4 to 1/2 tablet every 6 to 8 hours,not to exceed 1 1/2 tablets in 24 hours, or as directed by a doctor

Warnings

Do not use for children under 2 years of age unless directed by a doctor

Use

for prevention and treatment of these symptoms associated with motion sickness:

nauseavomitingdizziness

Ask a doctor before use if you have glaucoma; a breathing problem such as emphysema or chronic bronchitis; difficulty in urination due to an enlargement of the prostate gland.

Ask a doctor or pharmacist before use if you are taking sedatives or tranquilizers

When using this product: do not exceed recommended dosage; marked drowsiness may occur; avoid alcoholic drinks; alcohol, sedatives, and tranquilizers may increase drowsiness. Be careful when driving a motor vehicle or operating machinery.

PREGNANCY OR BREAST FEEDING

If pregnant or breast-feeding, ask a health professional before use.